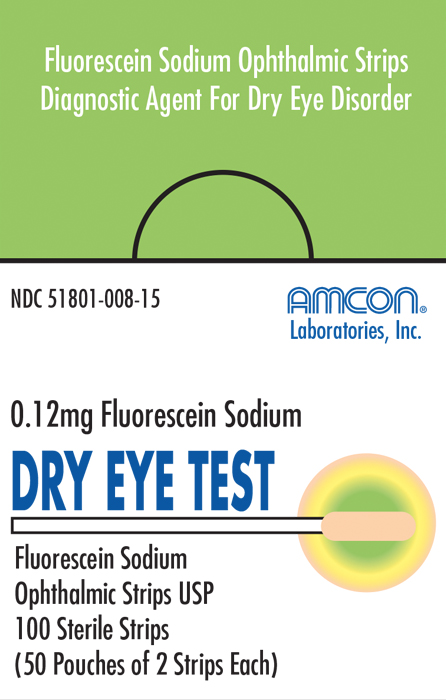 DRUG LABEL: Dry Eye Test
NDC: 51801-008 | Form: STRIP
Manufacturer: Nomax Inc.
Category: prescription | Type: HUMAN PRESCRIPTION DRUG LABEL
Date: 20191223

ACTIVE INGREDIENTS: Fluorescein Sodium 0.12 mg/1 1

Dry Eye Test

Dry Eye Test Fluorescein Sodium Ophthalmic Strips U.S.P. diagnostic agent is for professional use only

Each strip is impregnated with 0.12 mg of fluorescein sodium USP.

INDICATIONS

For testing tear film stability by determining the fluorescein break-up time (FBUT).

CONTRAINDICATIONS

Hypersensitivity to components or mercury-containing compounds.

DIRECTIONS FOR USE

Procedure for measuring Fluorescein

Break-up Time (FBUT) with Amcon Dry Eye Test Strips.

1. Apply one or two drops of non-preserved saline to the

impregnated paper tip. Excess fluid will automatically fall off.

Shaking is neither

required nor desirable.

2. Ask the patient to look down and in.

3. Gently touch the strip to the superior temporal bulbar conjunctiva

for one or two seconds.

4. Ask the patient to blink three times and open eyes naturally.

5. Conduct the FBUT measurements immediately.

6. Perform two consecutive measurements. If not consistent, conduct

a third and average the results.

7. Repeat steps 1 through 6 using a new strip for the second eye

FBUT values of less than 10 seconds are considered abnormal. Values less than 5 seconds are indicative of dry eye disorder. Values of 5 to 9 seconds are borderline dry eye.

NOTE: The contents may not be sterile if the individual strip package has been damaged or previously opened. This product is intended for external use only. Keep out of reach of children. Store below 30°C.

HOW SUPPLIED

Carton of 50 pouches of two strips each.

Nomax, Inc. • St. Louis, MO 63123 USA

Rev. 12/13
MSN 015-153